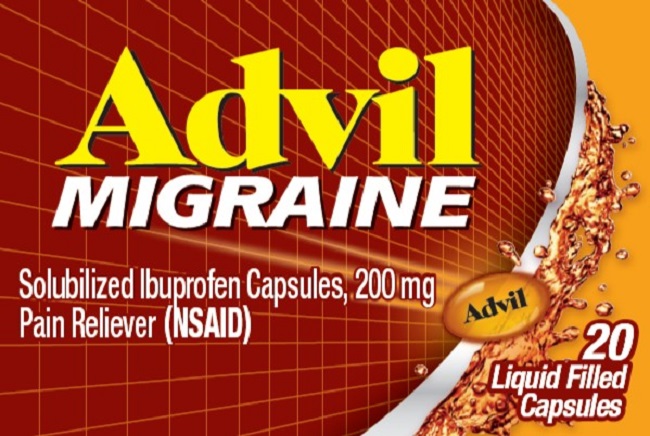 DRUG LABEL: ADVIL MIGRAINE
NDC: 0573-0168 | Form: CAPSULE, LIQUID FILLED
Manufacturer: Haleon US Holdings LLC
Category: otc | Type: HUMAN OTC DRUG LABEL
Date: 20251003

ACTIVE INGREDIENTS: IBUPROFEN 200 mg/1 1
INACTIVE INGREDIENTS: D&C YELLOW NO. 10; FD&C GREEN NO. 3; FD&C RED NO. 40; GELATIN, UNSPECIFIED; LIGHT MINERAL OIL; POLYETHYLENE GLYCOL, UNSPECIFIED; POTASSIUM HYDROXIDE; WATER; SORBITAN; SORBITOL

Drug Facts

Active ingredient (in each brown oval capsule)

Solubilized ibuprofen equal to 200 mg ibuprofen (NSAID)*

(present as the free acid and potassium salt)

*nonsteroidal anti-inflammatory drug

Purpose

Pain reliever

Use

- treats migraine

Warnings

Allergy alert:

Ibuprofen may cause a severe allergic reaction, especially in people allergic to aspirin. Symptoms may include:

- hives
- facial swelling
- asthma (wheezing)
- shock
- skin reddening
- rash
- blisters

If an allergic reaction occurs, stop use and seek medical help right away.

Stomach bleeding warning:

This product contains an NSAID, which may cause severe stomach bleeding. The chance is higher if you

- are age 60 or older
- have had stomach ulcers or bleeding problems
- take a blood thinning (anticoagulant) or steroid drug
- take other drugs containing prescription or nonprescription NSAIDs [aspirin, ibuprofen, naproxen, or others]
- have 3 or more alcoholic drinks every day while using this product
- take more or for a longer time than directed

Heart attack and stroke warning:

NSAIDs, except aspirin, increase the risk of heart attack, heart failure, and stroke. These can be fatal. The risk is higher if you use more than directed or for longer than directed.

Medication overuse headache warning:

Headaches may worsen if this product is used for 10 or more days per month.

Do not use

- if you have ever had an allergic reaction to any other pain reliever/fever reducer
- right before or after heart surgery

Ask a doctor before use if

- you have never had migraines diagnosed by a health professional
- you have a headache that is different from your usual migraines
- you have the worst headache of your life
- you have fever and stiff neck
- you have headaches beginning after or caused by head injury, exertion, coughing or bending
- you have experienced your first headache after the age of 50
- you have daily headaches
- you have a migraine so severe as to require bed rest
- stomach bleeding warning applies to you
- you have problems or serious side effects from taking pain relievers or fever reducers
- you have a history of stomach problems, such as heartburn
- you have high blood pressure, heart disease, liver cirrhosis, kidney disease, asthma, or had a stroke
- you are taking a diuretic

Ask a doctor or pharmacist before use if you are

- under a doctor's care for any serious condition
- taking aspirin for heart attack or stroke, because ibuprofen may decrease this benefit of aspirin
- taking any other drug

When using this product

- take with food or milk if stomach upset occurs

Stop use and ask a doctor if

- you experience any of the following signs of stomach bleeding:
  - feel faint
  - vomit blood
  - have bloody or black stools
  - have stomach pain that does not get better
- you have symptoms of heart problems or stroke:
  - chest pain
  - trouble breathing
  - weakness in one part or side of body
  - slurred speech
  - leg swelling
- migraine headache pain is not relieved or gets worse after the first dose
- any new symptoms appear

If pregnant or breast-feeding,

ask a health professional before use. It is especially important not to use ibuprofen at 20 weeks or later in pregnancy unless definitely directed to do so by a doctor because it may cause problems in the unborn child or complications during delivery.

Keep out of reach of children.

In case of overdose, get medical help or contact a Poison Control Center right away.

Directions

- do not take more than directed
- the smallest effective dose should be used
- adults: take 2 capsules with a glass of water; if symptoms persist or worsen, ask your doctor; do not take more than 2 capsules in 24 hours, unless directed by a doctor
- under 18 years of age: ask a doctor

Other information

- each capsule contains: potassium 20 mg
- read all directions and warnings before use. Keep carton.
- store at 20-25°C (68-77°F)
- avoid excessive heat above 40°C (104°F)

Inactive ingredients

D&C yellow no. 10, FD&C green no. 3, FD&C red no. 40, gelatin, pharmaceutical ink, polyethylene glycol, potassium hydroxide, purified water, sorbitol sorbitan solution

Questions or Comments?

Call toll-free 1-800-88-ADVIL

Additional Information

READ AND KEEP CARTON FOR COMPLETE
WARNINGS AND INFORMATION

Do Not Use if seal under bottle cap imprinted with “SEALED for YOUR PROTECTION” is broken or missing.

For most recent product information, visit www.Advil.com

PRINCIPAL DISPLAY PANEL

Advil
MIGRAINE

Solubilized Ibuprofen Capsules, 200 mg
Pain Reliever (NSAID)

20
Liquid Filled
Capsules

000068423 Front Carton